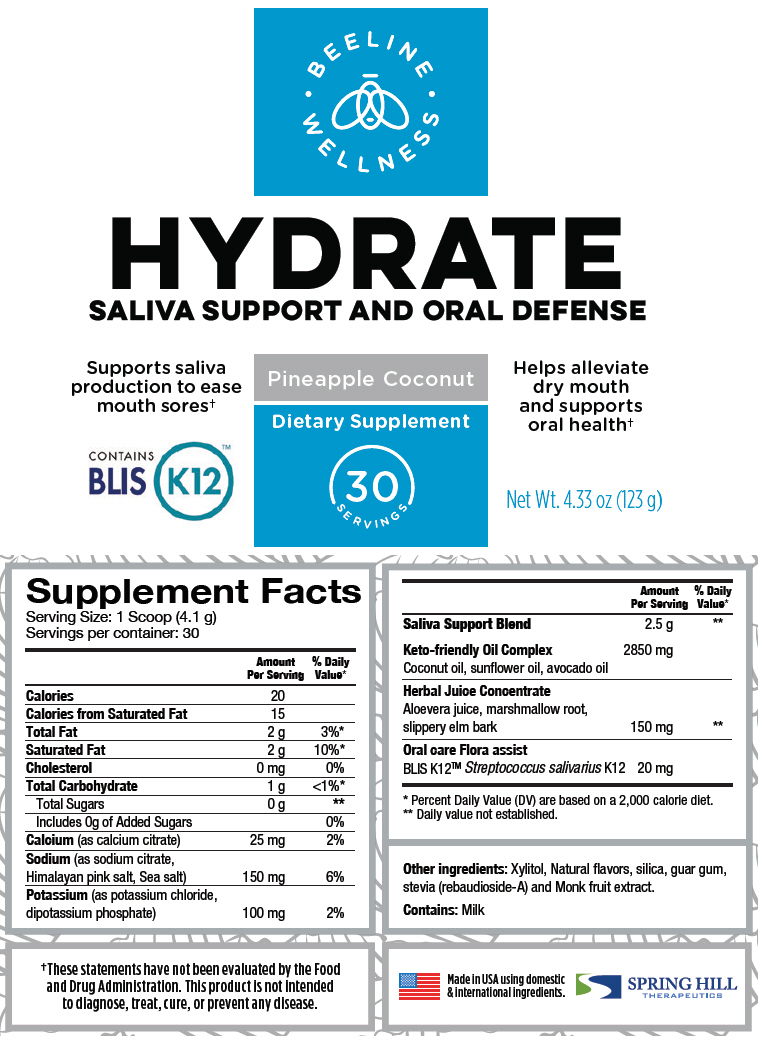 DRUG LABEL: Hydrate
NDC: 69833-020 | Form: POWDER, FOR SOLUTION
Manufacturer: Spring Hill Therapeutics LLC
Category: other | Type: DIETARY SUPPLEMENT
Date: 20200831

ACTIVE INGREDIENTS: calcium citrate 25 mg/4.1 g; sodium citrate, unspecified form 150 mg/4.1 g; sea salt 150 mg/4.1 g; potassium chloride 100 mg/4.1 g; dibasic potassium phosphate 100 mg/4.1 g; Coconut oil 2850 mg/4.1 g; sunflower oil 2850 mg/4.1 g; avocado oil 2850 mg/4.1 g; Aloe vera leaf 150 mg/4.1 g; althaea officinalis root 150 mg/4.1 g; ulmus rubra bark 150 mg/4.1 g; Streptococcus salivarius 20 mg/4.1 g
INACTIVE INGREDIENTS: Xylitol; silicon dioxide; guar gum; rebaudioside A

HYDRATE SALIVA SUPPORT AND ORAL DEFENSE

STATEMENT OF IDENTITY

Supplement Facts
Serving Size: 1 Scoop (4.1 g)
Servings per container: 30
 | Amount Per Serving | % Daily Value [Percent Daily Value (DV) are based on a 2,000 calorie diet.]
Calories | 20
Calories from Saturated Fat | 15
Total Fat | 2 g | 3%
Saturated Fat | 2 g | 10%
Cholesterol | 0 mg | 0%
Total Carbohydrate | 1 g | <1%
Total Sugars | 0 g | [Daily value not established.]
Includes 0g of Added Sugars |  | 0%
Calcium (as calcium citrate) | 25 mg | 2%
Sodium (as sodium citrate, Himalayan pink salt, Sea salt) | 150 mg | 6%
Potassium (as potassium chloride, dipotassium phosphate) | 100 mg | 2%
Saliva Support Blend | 2.5 g
Keto-friendly Oil Complex | 2850 mg
Coconut oil, sunflower oil, avocado oil
Herbal Juice Concentrate
Aloevera juice, marshmallow root, slippery elm bark | 150 mg
Oral care Flora assist
BLIS K12™ Streptococcus salivarius K12 | 20 mg

Other ingredients: Xylitol, Natural flavors, silica, guar gum, stevia (rebaudioside-A) and Monk fruit extract.

Contains: Milk

HEALTH CLAIM

†These statements have not been evaluated by the Food and Drug Administration. This product is not intended to diagnose, treat, cure, or prevent any disease.

Made in USA using domestic & international ingredients.

SPRING HILL
THERAPEUTICS

PRINCIPAL DISPLAY PANEL - 123 g Canister Label

• BEELINE •
WELLNESS

HYDRATE
SALIVA SUPPORT AND ORAL DEFENSE

Supports saliva
production to ease
mouth sores†

CONTAINS
BLIS
K12™

Pineapple Coconut

Dietary Supplement

30
SERVINGS

Helps alleviate
dry mouth
and supports
oral health†

Net Wt. 4.33 oz (123 g)